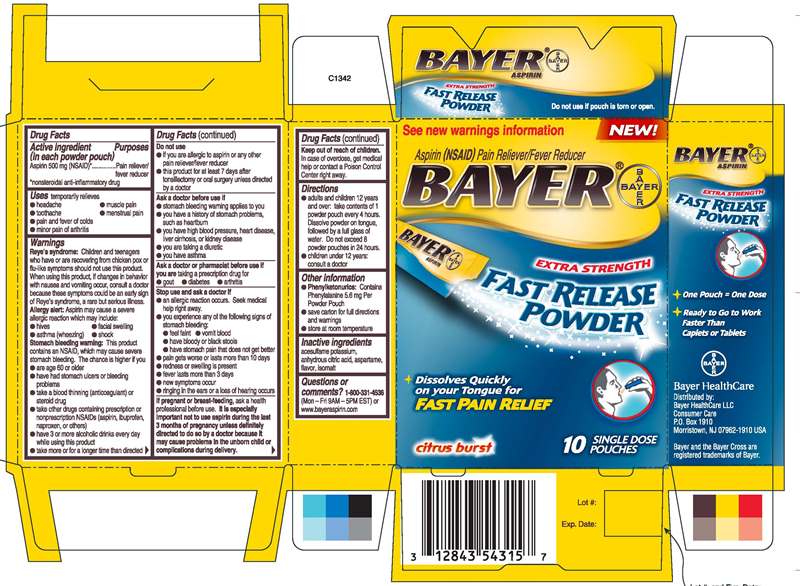 DRUG LABEL: BAYER 500 mg
NDC: 0280-0029 | Form: POWDER
Manufacturer: Bayer HealthCare LLC
Category: otc | Type: HUMAN OTC DRUG LABEL
Date: 20250117

ACTIVE INGREDIENTS: ASPIRIN 500 mg/1 1
INACTIVE INGREDIENTS: ASPARTAME; ACESULFAME POTASSIUM

BAYER 500 mg powder (Aspirin 500 mg powder)

ACTIVE INGREDIENT

Acetylsalicylic Acid 500mg